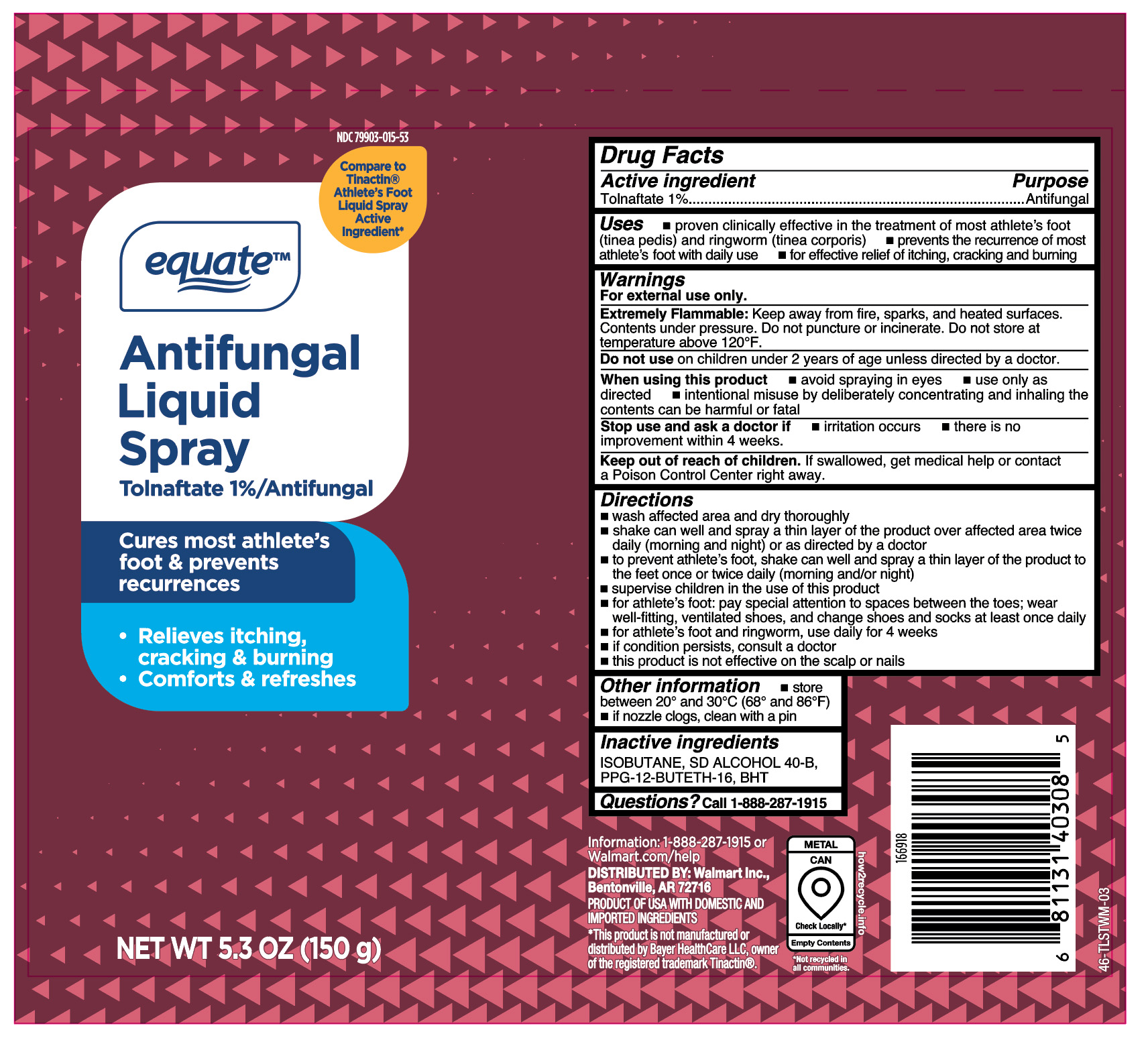 DRUG LABEL: Tolnaftate
NDC: 79903-015 | Form: AEROSOL, SPRAY
Manufacturer: Wal-Mart Stores, Inc
Category: otc | Type: HUMAN OTC DRUG LABEL
Date: 20260120

ACTIVE INGREDIENTS: TOLNAFTATE 1.5 g/150 g
INACTIVE INGREDIENTS: BUTYLATED HYDROXYTOLUENE; ISOBUTANE; PPG-12-BUTETH-16; ALCOHOL

Equate Antifungal Liquid Spray Tolnaftate 1%

Active ingredient

Tolnaftate 1%

Purpose

Antifungal

Uses

- proven clinically effective in the treatment of most athlete's foot (tinea pedis) and ringworm (tinea corporis)
- prevents the recurrence of most athlete's foot with daily use
- for effective relief of itching, cracking and burning

Warnings

For external use only.

Extremely Flammable:

Keep away from fire, sparks, and heated surfaces. Contents under pressure. Do not puncture or incinerate. Do not store at temperature above 120°F.

Do not use

on children under 2 years of age unless directed by a doctor.

When using this product

- avoid spraying in eyes
- use only as directed
- intentional misuse by deliberately concentrating and inhaling the contents can be harmful or fatal

Stop use and ask a doctor if

- irritation occurs
- there is no improvement within 4 weeks

Keep out of reach of children.

If swallowed, get medical help or contact a Poison Control Center right away.

Directions

- wash affected area and dry thoroughly
- shake can well and spray a thin layer of the product over affected area twice daily (morning and night) or as directed by a doctor
- to prevent athlete’s foot, shake can well and spray a thin layer of the product to the feet once or twice daily (morning and/or night)
- supervise children in the use of this product
- for athlete's foot: pay special attention to spaces between the toes; wear well-fitting, ventilated shoes, and change shoes and socks at least once daily
- for athlete's foot and ringworm, use daily for 4 weeks
- if condition persists, consult a doctor
- this product is not effective on the scalp or nails

Other information

- store between 20º and 30ºC (68º and 86ºF)
- if nozzle clogs, clean with a pin

Inactive ingredients

ISOBUTANE, SD ALCOHOL 40-B, PPG-12-BUTETH-16, BHT

Questions?

1-888-287-1915

Principal Display Panel

equate

Antifungal

Liquid

Spray

Tolnaftate 1%/Antifungal

Cures most athlete's

foot & prevents

recurrences

- Relieves itching,

cracking & burning

- Comforts & refreshes

NET WT 5.3 OZ (150g)